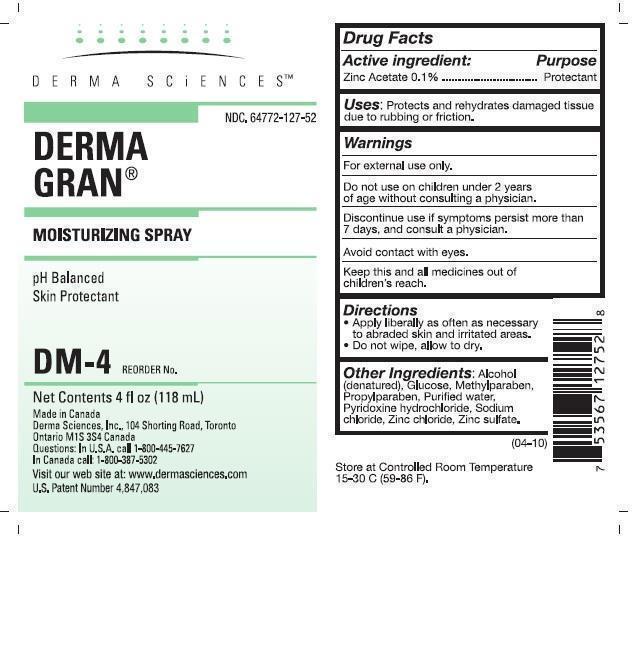 DRUG LABEL: DERMA GRAN
                
NDC: 64772-127 | Form: SPRAY
Manufacturer: Derma Sciences Canada, Inc.
Category: otc | Type: HUMAN OTC DRUG LABEL
Date: 20150420

ACTIVE INGREDIENTS: ZINC ACETATE 0.1 g/100 g
INACTIVE INGREDIENTS: ALCOHOL; DEXTROSE; METHYLPARABEN; PROPYLPARABEN; WATER; PYRIDOXINE HYDROCHLORIDE; SODIUM CHLORIDE; ZINC CHLORIDE; ZINC SULFATE

Drug Facts

Active ingredient:

Zinc Acetate 0.1%

Purpose

Protectant

Uses:

Protects and rehydrates damaged tissue due to rubbing or friction.

Warnings

For external use only.

Do not use on

children under 2 years of age without consulting a physician.

STOP USE

Discontinue use if symptoms persist more than 7 days, and consult a physician.

Avoid contact with eyes.

KEEP OUT OF REACH OF CHILDREN

Keep this and all medicines out of children's reach.

Directions

- Apply liberally as often as necessary to abraded skin and irritated areas.
- Do not wipe, allow to dry.

Other Ingredients:

Alcohol (denatured), Glucose, Methylparaben, Propylparaben, Purified water, Pyridoxine hydrochloride, Sodium chloride, Zinc chloride, Zinc sulfate.

Store at Controlled Room Temperature 15-30 C (59-86 F).

Principal Display Panel

DERMA SCiENCES™

NDC 64772-127-52

DERMA GRAN®

MOISTURIZING SPRAY

pH Balanced

Skin Protectant

DM-4

REORDER No.

Net Contents 4 fl oz (118 mL)

Made in Canada

Derma Sciences, Inc., 104 Shorting Road, Toronto

Ontario M1S 3S4 Canada

Questions: In U.S.A. call 1-800-445-7627

In Canada call: 1-800-387-5302

Visit our web site at: www.dermasciences.com

U.S. Patent Number 4,847,083